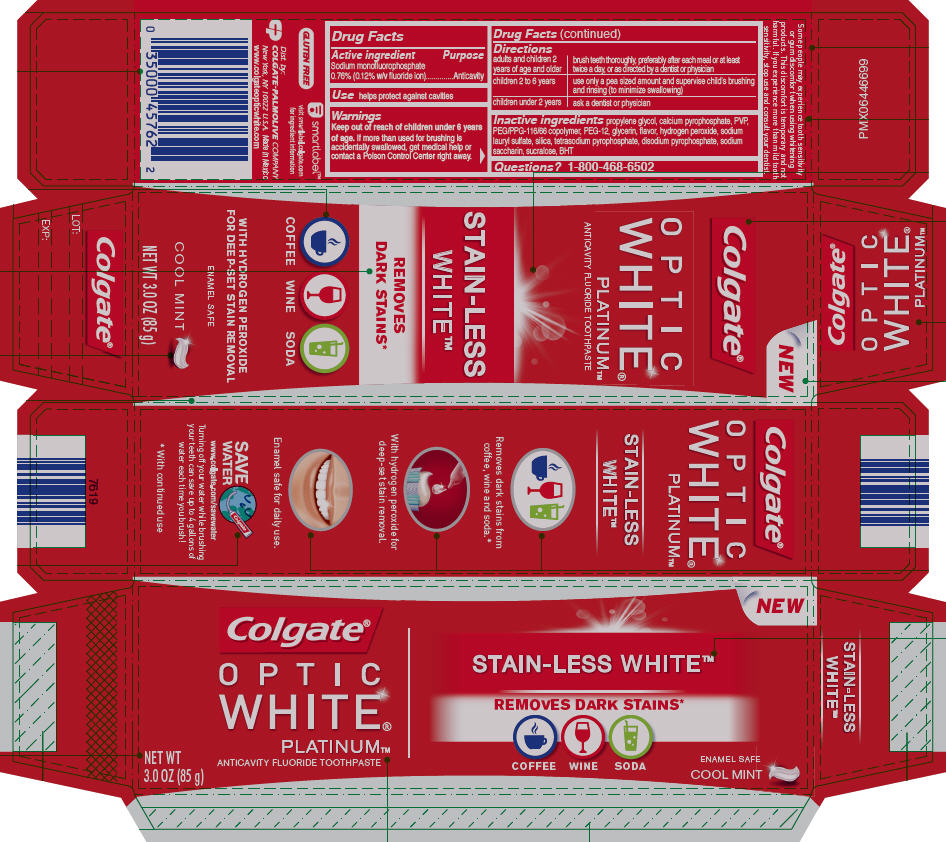 DRUG LABEL: Colgate Optic White Platinum Stain-Less
NDC: 35000-973 | Form: PASTE, DENTIFRICE
Manufacturer: Colgate-Palmolive Company
Category: otc | Type: HUMAN OTC DRUG LABEL
Date: 20191219

ACTIVE INGREDIENTS: SODIUM MONOFLUOROPHOSPHATE 1 mg/1 g
INACTIVE INGREDIENTS: PROPYLENE GLYCOL 399.8 mg/1 g; CALCIUM PYROPHOSPHATE; POVIDONE K15; PEG/PPG-116/66 COPOLYMER; POLYETHYLENE GLYCOL 600; GLYCERIN; HYDROGEN PEROXIDE; SODIUM LAURYL SULFATE; SILICON DIOXIDE; SODIUM PYROPHOSPHATE; SODIUM ACID PYROPHOSPHATE; SACCHARIN SODIUM; SUCRALOSE; BUTYLATED HYDROXYTOLUENE

Colgate® Optic White® Platinum™ Stain-Less Toothpaste

Drug Facts

Active ingredient

Sodium monofluorophosphate 0.76% (0.12% w/v fluoride ion)

Purpose

Anticavity

Use

helps protect against cavities

Warnings

Keep out of reach of children under 6 years of age. If more than used for brushing is accidentally swallowed, get medical help or contact a Poison Control Center right away.

Directions

adults and children 2 years of age and older | brush teeth thoroughly, preferably after each meal or at least twice a day, or as directed by a dentist or physician
children 2 to 6 years | use only a pea sized amount and supervise child's brushing and rinsing (to minimize swallowing)
children under 2 years | ask a dentist or physician

Inactive ingredients

propylene glycol, calcium pyrophosphate, PVP, PEG/PPG-116/66 copolymer, PEG-12, glycerin, flavor, hydrogen peroxide, sodium lauryl sulfate, silica, tetrasodium pyrophosphate, disodium pyrophosphate, sodium saccharin, sucralose, BHT

Questions?

1-800-468-6502

Dist. by:
COLGATE-PALMOLIVE COMPANY
New York, NY 10022 U.S.A.

PRINCIPAL DISPLAY PANEL - 85 g Tube Carton

Colgate®

OPTIC
WHITE®

PLATINUM™
ANTICAVITY FLUORIDE TOOTHPASTE

NET WT
3.0 OZ (85 g)

NEW

STAIN-LESS WHITE™

REMOVES DARK STAINS*

COFFEE
WINE
SODA

ENAMEL SAFE

COOL MINT